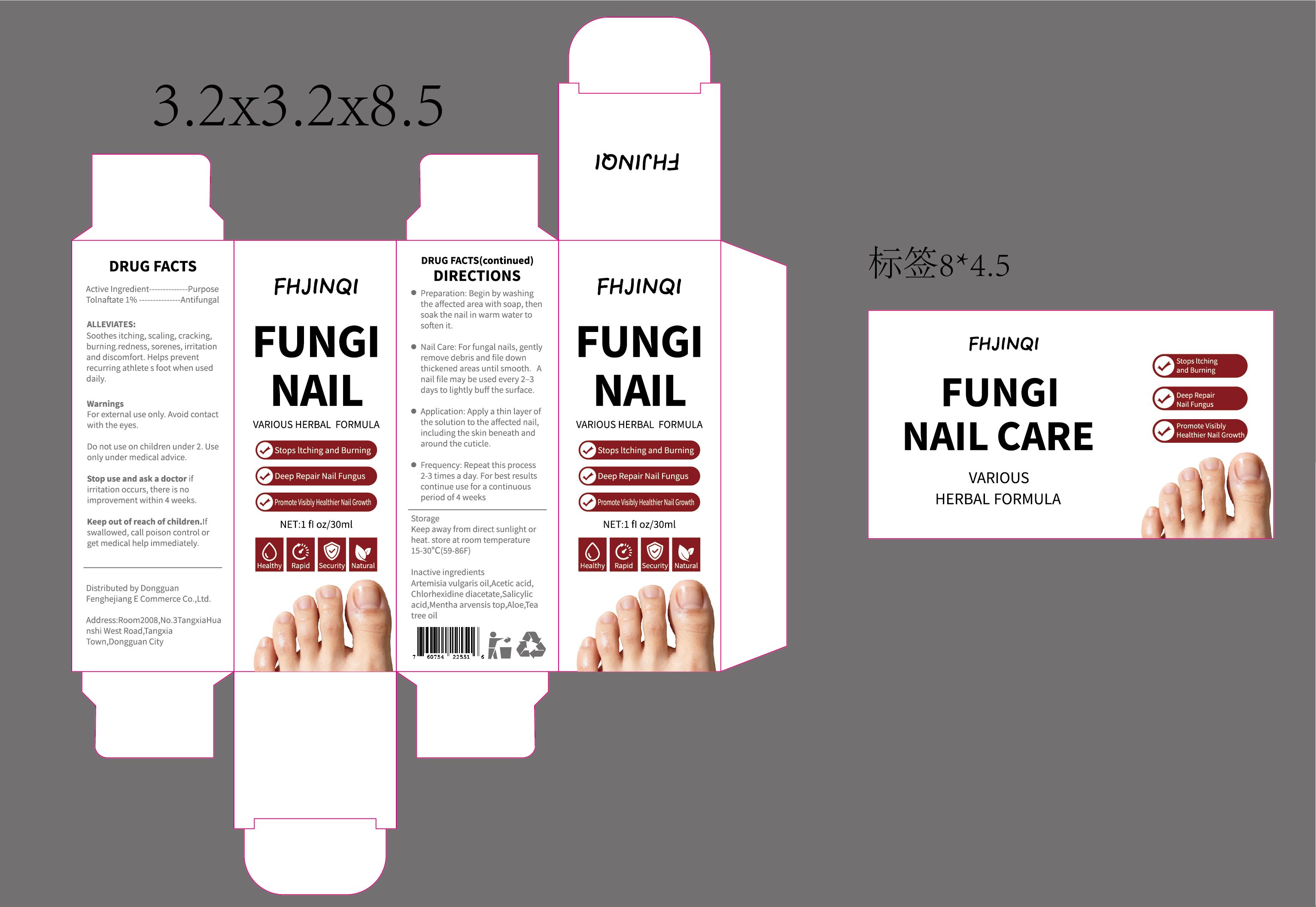 DRUG LABEL: FHJINQI  FUNGI NAIL CARE
NDC: 85960-002 | Form: LIQUID
Manufacturer: Dongguan Fenghejiang E Commerce Co., Ltd.
Category: otc | Type: HUMAN OTC DRUG LABEL
Date: 20251204

ACTIVE INGREDIENTS: TOLNAFTATE 1 g/100 mL
INACTIVE INGREDIENTS: ARTEMISIA VULGARIS OIL; ACETIC ACID; TEA TREE OIL; CHLORHEXIDINE DIACETATE; SALICYLIC ACID; MENTHA ARVENSIS TOP; ALOE

Active Ingredient：Tolnaftate 1%

PURPOSE

Stops ltching and Burning
Deep Repair Nail Fungus

Keep out of reach of children.lfswallowed, call poison control orget medical help immediately.

INACTIVE INGREDIENT

ARTEMISIA VULGARIS OIL
ACETIC ACID
CHLORHEXIDINE DIACETATESALICYLIC ACID
MENTHA ARVENSIS TOP
ALOE
TEA TREE OIL

INDICATIONS AND USAGE

Preparation: Begin by washingthe affected area with soap, thensoak the nail in warm water tosoften it.
Nail Care: For fungal nails, gentlyremove debris and file downthickened areas until smooth. Anail file may be used every 2-3days to lightly buff the surface.
Application: Apply a thin layer ofthe solution to the affected nail.including the skin beneath andaround the cuticle.

DOSAGE AND ADMINISTRATION

Frequency: Repeat this process2-3 times a day. For best resultscontinue use for a continuousperiod of 4 weeks

WARNINGS

WarningsFor external use only. Avoid contactwith the eyes.
Do not use on children under 2.Useonly under medical advice.
Stop use and ask a doctor ifirritation occurs, there is noimprovement within 4 weeks